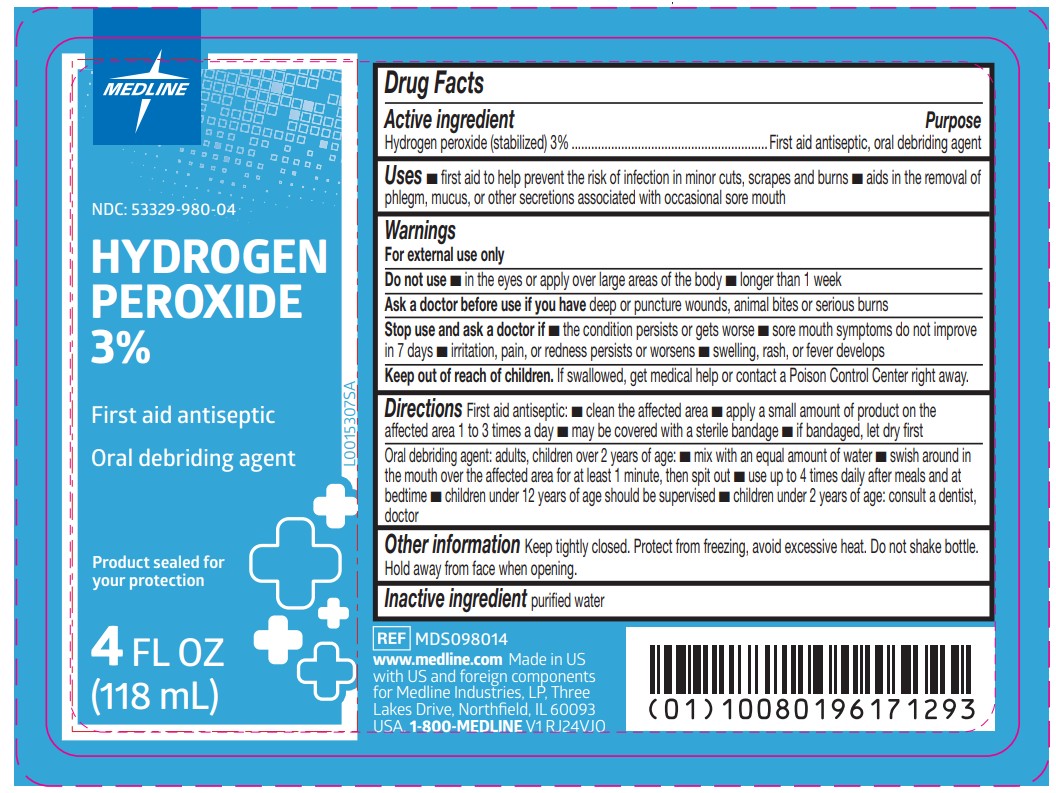 DRUG LABEL: Hydrogen peroxide
NDC: 53329-980 | Form: SOLUTION
Manufacturer: Medline Industries, LP
Category: otc | Type: HUMAN OTC DRUG LABEL
Date: 20260211

ACTIVE INGREDIENTS: HYDROGEN PEROXIDE 3 mL/100 mL
INACTIVE INGREDIENTS: WATER

980 Hydrogen Peroxide Solution

Active ingredient

Hydrogen peroxide (stabilized) 3%

Purpose

First aid antiseptic

Oral debriding agent

Uses

- first aid to help prevent the risk of infection in minor cuts,scrapes and burns
- aids in the removal of phlegm, mucus, or other secretions associated with occasional sore mouth

Warnings

For external use only

Do not use

- in the eyes or apply over large areas of the body
- longer than 1 week

Ask a doctor before use if you have

deep or puncture wounds, animal bites or serious burns

Stop use and ask a doctor if

- the condition persists or gets worse
- sore mouth symptoms do not improve in 7 days
- irritation, pain, or redness persists or worsens
- swelling, rash, or fever develops

Keep out of reach of children.

If swallowed, get medical help or contact a Poison Control Center right away.

Directions

First aid antiseptic:

- clean the affected area
- apply a small amount of product on the affected area 1 to 3 times a day
- may be covered with a sterile bandage
- if bandaged, let dry first

Oral debriding agent: adults, children over 2 years of age:

- mix with an equal amount of water
- swish around in the mouth over the affected area for at least 1 minute, then spit out
- use up to 4 times daily after meals and at bedtime
- children under 12 years of age should be supervised in the use
- children under 2 years of age: consult a dentist, doctor

Other information

Keep tightly closed. Protect from freezing, avoid excessive heat. Do not shake bottle. Hold away from face when opening.

Inactive ingredient

purified water

Manufacturing Information

Made in US with US and foreign components for:
Medline Industries, LP
Three Lakes Drive, Northfield, IL 60093 USA
www.medline.com
1-800-MEDLINE (633-5463)
REF: MDS098014